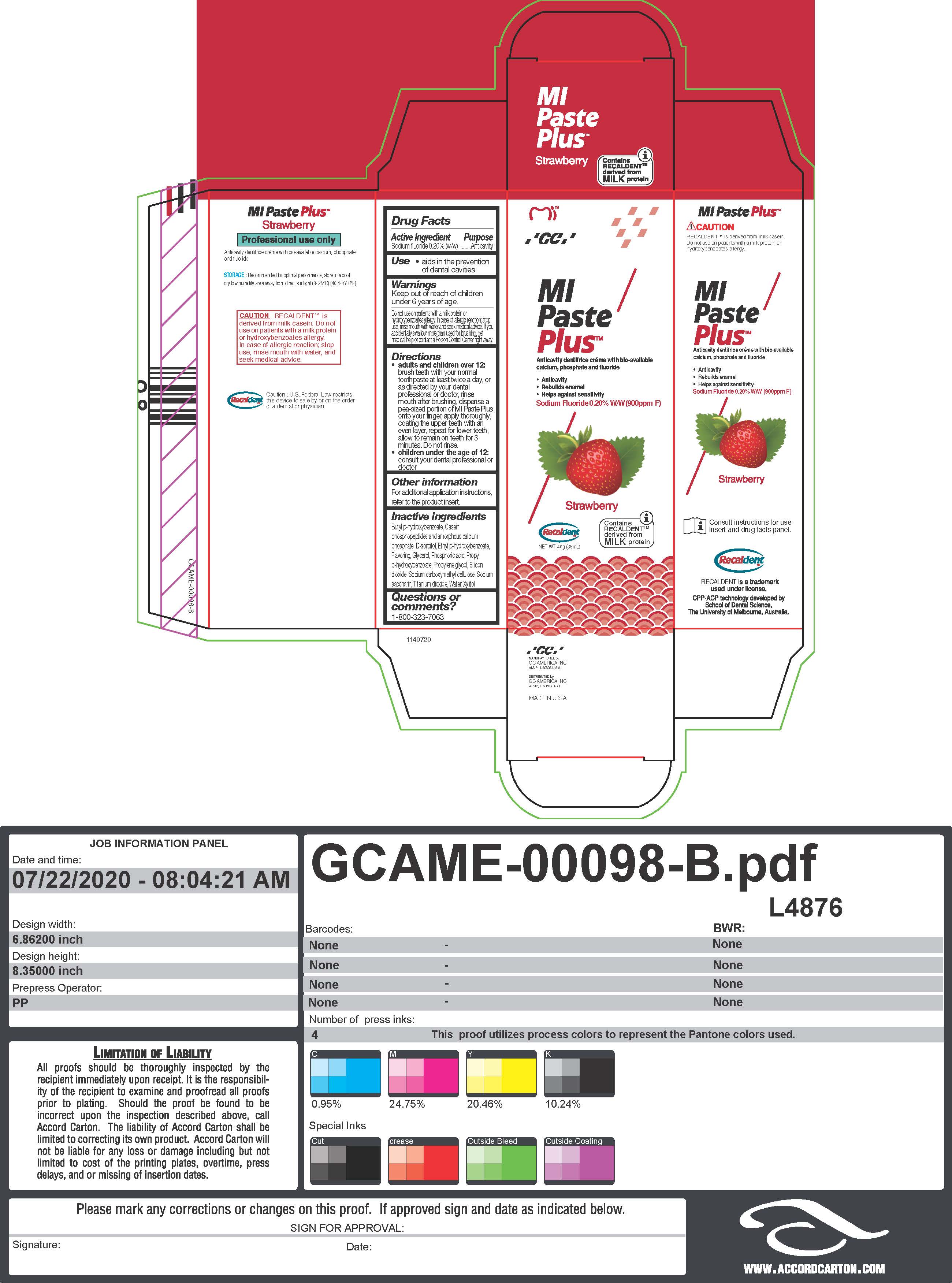 DRUG LABEL: MIPaste Plus Strawberry
NDC: 61596-800 | Form: PASTE, DENTIFRICE
Manufacturer: GC America Inc.
Category: otc | Type: HUMAN OTC DRUG LABEL
Date: 20251219

ACTIVE INGREDIENTS: SODIUM FLUORIDE 0.2 g/100 g
INACTIVE INGREDIENTS: SACCHARIN SODIUM; CARBOXYMETHYLCELLULOSE SODIUM, UNSPECIFIED FORM; CALCIUM PHOSPHATE, UNSPECIFIED FORM; SORBITOL; ETHYLPARABEN; PHOSPHORIC ACID; PROPYLENE GLYCOL; TITANIUM DIOXIDE; SILICON DIOXIDE; XYLITOL; WATER; BUTYLPARABEN; GLYCERIN; PROPYLPARABEN

MIPaste Plus Strawberry (2)

Active Ingredient
Sodium fluoride 0.20% (w/w)

INDICATIONS AND USAGE

aids in the prevention of dental cavities

Warnings
Keep out of reach of children under 6 years of age. Do not use on patients with a milk protein or hydroxybenzoates allergy. In case of allergic reaction; stop use, rinse mouth with water and seek medical advice. If you accidentally swallow more than used for brushing, get medical help or contact a Poison Control Center right away

Directions
• adults and children over 12:
brush teeth with your normal
toothpaste at least twice a day, or
as directed by your dental
professional or doctor, rinse
mouth after brushing, dispense a
pea-sized portion of MI Paste Plus
onto your finger, apply thoroughly,
coating the upper teeth with an
even layer, repeat for lower teeth,
allow to remain on teeth for 3
minutes. Do not rinse.
• children under the age of 12:
consult your dental professional or
doctor

Inactive ingredients
Butyl p-hydroxybenzoate, Casein
phosphopeptides and amorphous calcium
phosphate, D-sorbitol, Ethyl p-hydroxybenzoate,
Flavoring, Glycerol, Phosphoric acid, Propyl
p-hydroxybenzoate, Propylene glycol, Silicon
dioxide, Sodium carboxymethyl cellulose, Sodium saccharin, Titanium dioxide, Water, Xylitol

Keep out of reach of children
under 6 years of age.

Purpose

Anticavity